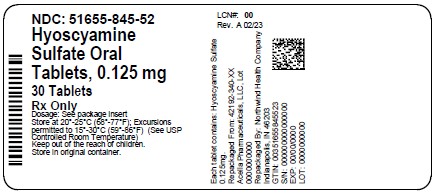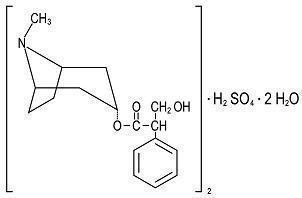 DRUG LABEL: Hyoscyamine Sulfate TAB
NDC: 51655-845 | Form: TABLET
Manufacturer: Northwind Health Company, LLC
Category: prescription | Type: HUMAN PRESCRIPTION DRUG LABEL
Date: 20260101

ACTIVE INGREDIENTS: HYOSCYAMINE SULFATE 0.125 mg/1 1
INACTIVE INGREDIENTS: D&C YELLOW NO. 10; FD&C BLUE NO. 1; LACTOSE MONOHYDRATE; MAGNESIUM STEARATE; MANNITOL; STARCH, CORN; STEARIC ACID

Hyoscyamine Sulfate Tab
Oral Tablets
Rx Only

DESCRIPTION

Each round, green, peppermint flavored tablet, for oral administration contains:

Hyoscyamine Sulfate, USP …… 0.125 mg.

Hyoscyamine sulfate is one of the principal anticholinergic/ antispasmodic components of belladonna alkaloids.

(C17H23NO3)2• H2SO4• 2H2O M.W. = 712.85

INACTIVE INGREDIENTS

Inactive ingredients include:Green LKB #LB-620, lactose monohydrate, magnesium stearate (veg), mannitol USP, peppermint flavor, starch and stearic acid.

CLINICAL PHARMACOLOGY

Hyoscyamine has actions similar to those of atropine, but is more potent in both its central and peripheral effects.

This product inhibits gastrointestinal propulsive motility and decreases gastric acid secretions. This product controls excessive pharyngeal, tracheal, and bronchial secretion. This product is absorbed totally and completely by sublingual administration as well as oral administration.

Once absorbed, this product disappears rapidly from the blood and is distributed throughout the entire body.

The majority of hyoscyamine sulfate is excreted in the urine unchanged within the first 12 hours and only traces of hyoscyamine sulfate are found in the breast milk.

INDICATIONS AND USAGE

This product may be used in functional intestinal disorders to reduce symptoms such as those seen in mild dysenteries and diverticulitis. It can also be used to control gastric secretion, visceral spasm and hypermotility in cystitis, pylorospasm and associated abdominal cramps.

Along with appropriate analgesics, this product is indicated in symptomatic relief of biliary and renal colic and as a drying agent in the relief of symptoms of acute rhinitis.

This product is effective as adjunctive therapy in the treatment of peptic ulcer and irritable bowel syndrome, acute enterocolitis and other functional gastrointestinal disorders.

CONTRAINDICATIONS

Glaucoma, obstructive uropathy, obstructive diseases of the gastrointestinal tract, paralytic ileum, intestinal atony of elderly or debilitated patients, unstable cardiovascular status, severe ulcerative colitis, toxic megacolon, myasthenia gravis, and myocardial ischemia. This product is not recommended for use in children under twelve years of age.

WARNINGS

Heat prostration can occur with drug use in the event of high environmental temperature.

Diarrhea may be an early symptom of incomplete intestinal obstruction, especially in patients with ileostomy or colostomy; in this instance, treatment would be inappropriate and possibly harmful.

This product may cause drowsiness or blurred vision. Patients taking this product should be warned not to engage in activities requiring mental alertness such as operating a motor vehicle or other machinery or to perform hazardous tasks while taking this drug.

PRECAUTIONS

Use caution in patients with hiatal hernia associated with reflex esophagitis. Use extreme caution and only when needed in patients with autonomic neuropathy, hyperthyroidism, coronary heart disease, congestive heart failure and cardiac arrhythmia. Investigate any tachycardia before giving any anticholinergic drugs since they may increase the heart rate.

Prolonged use of anticholinergics may decrease or inhibit salivary flow, thus contributing to the development of caries, periodontal disease, oral candidiasis, and discomfort.

Information for Patients:

This medication should be taken 30 minutes to one hour before meals. This medication should be used with caution during exercise or hot weather; overheating may result in heat stroke. Hyoscyamine may cause drowsiness, dizziness or blurred vision; patients should observe caution before driving, using machinery or performing other tasks requiring mental alertness.

Drug Interactions:

Absorption of other oral medications may be decreased during concurrent use with anticholinergics due to decreased gastrointestinal motility and delayed gastric emptying. Drug interactions may occur when anticholinergics are used with the following medications: antacids, antidiarrheals (adsorbent), other anticholinergics, antimyasthenics, cyclopropane, haloperidol, ketoconazole, metoclopramide, opioid (narcotic) analgesics, and potassium chloride.

Pregnancy:

Pregnancy Category C.Animal reproduction studies have not been conducted with this product. It is also not known whether this product can cause fetal harm when administered to a pregnant woman or can affect reproduction capacity.

Hyoscyamine crosses the placenta. This product should be given to a pregnant woman only if clearly needed.

Nursing Mothers:

This product is excreted in human milk. This product should not be administered to a nursing mother.

Pediatric Use:

This product is not recommended for use in children under twelve years of age. Infants and young children are especially susceptible to the toxic effects of anticholinergics. Close supervision is recommended for infants and children with spastic paralysis or brain damage since an increased response to anticholinergics has been reported in these patients and dosage adjustments are often required.

When anticholinergics are given to children where the environmental temperature is high, there is a risk of a rapid increase in body temperature because of these medications’ suppression of sweat gland activity. A paradoxical reaction characterized by hyperexcitability may occur in children taking large doses of anticholinergics.

Geriatric Use:

Geriatric patients may respond to usual doses of anticholinergics with excitement, agitation, drowsiness, or confusion.

Geriatric patients are especially susceptible to the anticholinergic side effects, such as constipation, dryness of mouth, and urinary retention (especially in males). If these side effects occur and continue or are severe, medication should probably be discontinued. Caution is also recommended when anticholinergics are given to geriatric patients, because of the danger of precipitating undiagnosed glaucoma.

Memory may become severely impaired in geriatric patients, especially those who already have memory problems, with the continued use of anticholinergics since these drugs block the actions of acetylcholine, which is responsible for many functions of the brain, including memory functions.

ADVERSE REACTIONS

Not all of the following adverse reactions have been reported with hyoscyamine sulfate. The following adverse reactions have been reported for pharmacologically similar drugs with anticholinergic/ antispasmodic action. Adverse reactions may include dryness of the mouth, urinary hesitancy and retention; blurred vision; tachycardia; palpitations; mydriasis; cycloplegia; increased ocular tension; loss of taste; headache; nervousness; drowsiness; weakness; dizziness; insomnia; nausea; vomiting; impotence; suppression of lactation; constipation; bloated feeling; allergic reactions or drug idiosyncrasies; urticaria and other dermal manifestations; ataxia; speech disturbance; some degree of mental confusion and/or excitement (especially in elderly persons); and decreased sweating.

OVERDOSAGE

The signs and symptoms of overdose are headache, nausea, vomiting, blurred vision, dilated pupils, hot dry skin, dizziness, dryness of the mouth, difficulty in swallowing and CNS stimulation. Measures to be taken are immediate lavage of the stomach and injection of physostigmine 0.5 to 2 mg intravenously and repeated as necessary up to a total of 5 mg. Fever may be treated symptomatically (tepid water sponge baths, hypothermic blanket). Excitement to a degree which demands attention may be managed with sodium thiopental 2% solution given slowly intravenously or chloral hydrate (100- 200 mL of a 2% solution) by rectal infusion.

In the event of progression of the curare-like effect to paralysis of the respiratory muscles, artificial respiration should be instituted and maintained until effective respiratory action returns.

In rats, the LD50for hyoscyamine is 375 mg/kg. Hyoscyamine is dialyzable.

DOSAGE AND ADMINISTRATION

Dosage may be adjusted according to the condition and severity of symptoms. May be taken with or without water.

Adults and adolescents 12 years of age and older:1 to 2 tablets orally three or four times a day, thirty minutes to one hour before meals and at bedtime. Dosage may be increased to every four hours as needed. Do not exceed 12 tablets in 24 hours.

Note:Geriatric patients may be more sensitive to the effects of the usual adult dose.

HOW SUPPLIED

Hyoscyamine Sulfate TABis supplied as round, green, peppermint flavored tablets with "40" debossed on one side.They are available in bottles of 30 tablets, NDC 51655-845-52.

Storage and Handling

Dispense in a tight, light-resistant container as defined in USP/NF, with a child-resistant closure.

Store at controlled room temperature between 20°-25°C (68°-77°F), see USP Controlled Room Temperature.

KEEP THIS AND ALL MEDICATION OUT OF THE REACH OF CHILDREN. IN CASE OF ACCIDENTAL OVERDOSE, SEEK PROFESSIONAL ASSISTANCE OR CONTACT A POISON CONTROL CENTER IMMEDIATELY.

All prescription substitutions and/or recommendations using this product shall be made subject to state and federal statutes as applicable. Please NOTE: This is not an Orange Book product and has not been subjected to FDA therapeutic equivalency or other equivalency testing. No representation is made as to generic status or bioequivalency.Each person recommending a prescription substitution using this product shall make such recommendation based on his/her professional knowledge and opinion, upon evaluating the active ingredients, inactive ingredients, excipients and chemical information provided herein.

Distributed by:

Acella Pharmaceuticals, LLC
Alpharetta, GA 30022
1-800-541-4802

L-0402 Rev. 0723-01 0S42192340

Principal Display Panel

NDC: 51655-845-52